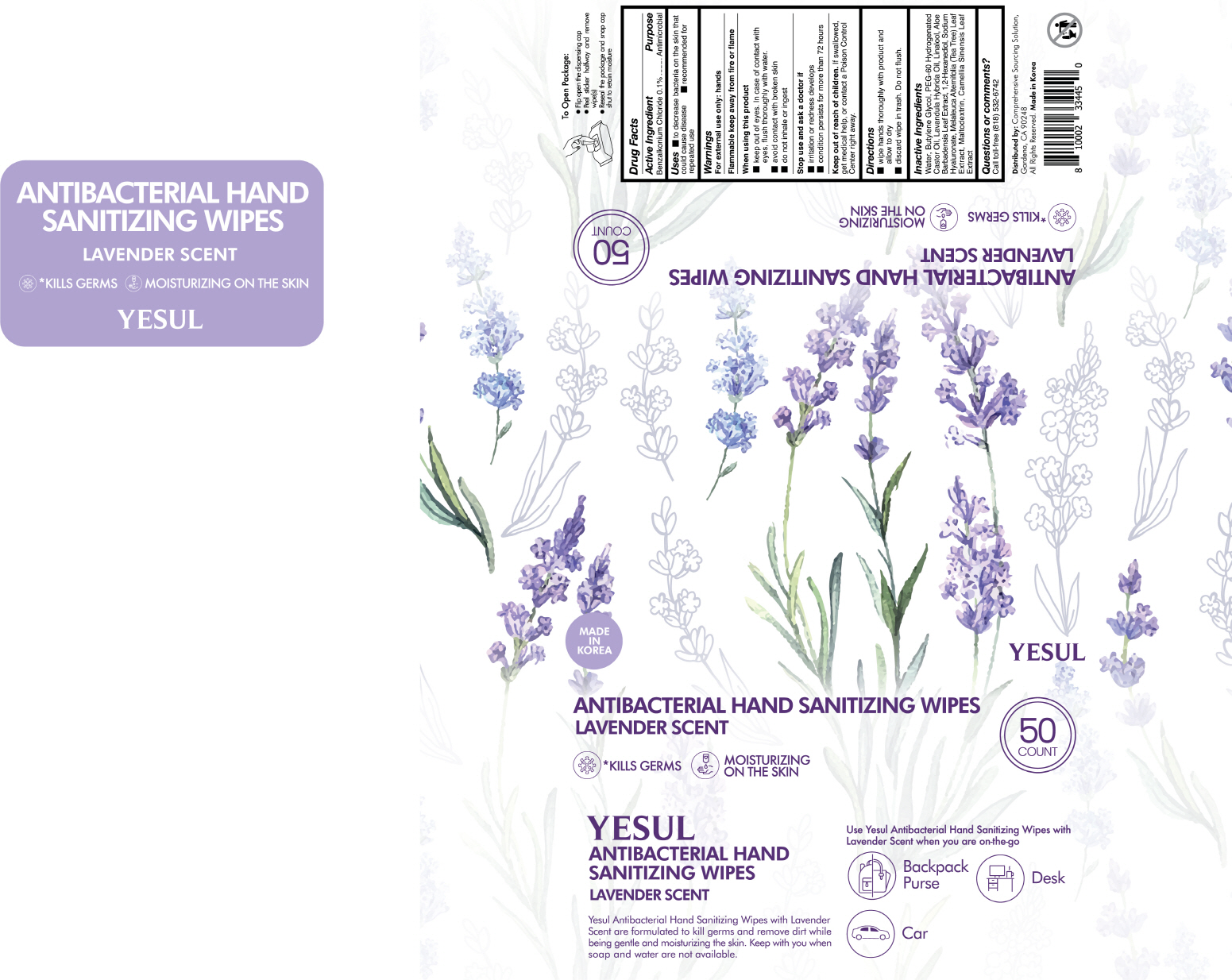 DRUG LABEL: YESUL ANTIBACTERIAL HAND SANITIZING WIPES LAVENDER SCENT
NDC: 76966-0024 | Form: CLOTH
Manufacturer: N Bridge Inc.
Category: otc | Type: HUMAN OTC DRUG LABEL
Date: 20200910

ACTIVE INGREDIENTS: BENZALKONIUM CHLORIDE 0.18 g/50 1
INACTIVE INGREDIENTS: LINALOOL, (+/-)-; LAVANDIN OIL; WATER; BUTYLENE GLYCOL; ALOE VERA LEAF; 1,2-HEXANEDIOL; HYALURONATE SODIUM; MELALEUCA ALTERNIFOLIA LEAF; MALTODEXTRIN; GREEN TEA LEAF; PEG-60 HYDROGENATED CASTOR OIL

ACTIVE INGREDIENT

Benzalkonium Chloride

INACTIVE INGREDIENT

Water, butylene glycol, peg-60 hydrogenated castor oil, lavandula hybrida oil, linalool, aloe barbadensis leaf extract, 1,2-hexanediol, sodium hyaluronate, melaleuca alternifolia (tea tree) leaf extract, maltodextrin, camellia sinensis leaf extract

PURPOSE

Antiseptic

keep out of reach of the children

INDICATIONS AND USAGE

wet hands thoroughly with product and allow to dry without wiping

for children under 6, use only under adult supervision

not recommended for infants

WARNINGS

For external use only. Flammable. Keep away from heat or flame.

Do not use

- in children less than 2 months of age
- on open skin wounds

When using this product keep out of eyes, ears, and mouth. In case of contact with eyes, rinse thoroughly with water.

Stop use and ask a doctor if irritation or rash occurs. These may be signs of a serious condition.

Keep out of reach of children. If swallowed, get medical help or contact a Poison Control Center right away.

DOSAGE AND ADMINISTRATION

for external use only